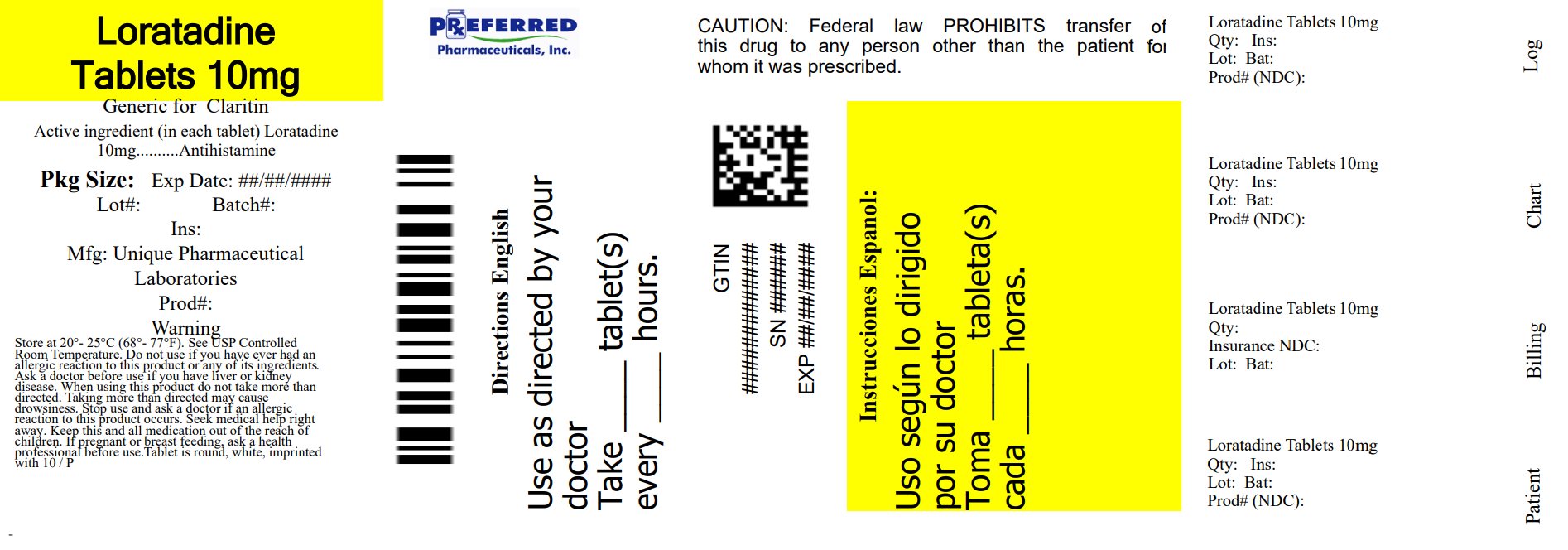 DRUG LABEL: Loratadine
NDC: 68788-8616 | Form: TABLET
Manufacturer: Preferred Pharmaceuticals Inc
Category: otc | Type: HUMAN OTC DRUG LABEL
Date: 20250723

ACTIVE INGREDIENTS: LORATADINE 10 mg/1 1
INACTIVE INGREDIENTS: LACTOSE MONOHYDRATE; MAGNESIUM STEARATE; POVIDONE, UNSPECIFIED; STARCH, CORN

Loratadine

Active Ingredient (in each tablet)

Loratadine, 10 mg USP

Purpose

Antihistamine

Uses

Temporarily relieves these symptoms due to hay fever or other respiratory allergies:

- runny nose
- sneezing
- itchy, watery eyes
- itching of the nose or throat

Warnings

Do not use if you ever have had an allergic reaction to this product or any of its ingredients.

Ask a doctor before use if you have liver or kidney disease. Your doctor should determine if you need a different dose.

When using this product do not take more than directed. Taking more than directed may cause drowsiness.

Stop use and ask a doctor if an allergic reaction to this product occurs. Seek medical help right away.

PREGNANCY OR BREAST FEEDING

If pregnanct or breast-feeding, ask a health professional before use.

Keep out of reach of children. In case of overdose, get medical help or contact a Poison Control Center right away.

Directions

adults and children 6 years of age and over | 1 tablet daily; not more than 1 tablet in 24 hours
children under 6 years of age | ask a doctor
consumers with liver or kidney disease | ask a doctor

Other Information

- Tamper-evident: do not use if foil seal under cap, printed with "SEALED for YOUR PROTECTION" is missing, open or broken.
- Store between 20° - 25°C (68°-77°F)

INACTIVE INGREDIENT

Inactive ingredients corn starch, lactose monohydrate, magnesium stearate, povidone

Questions or comments?

Call 1-800-874-7464 Monday to Friday 9 AM to 5 PM EST

PACKAGE LABEL.PRINCIPAL DISPLAY PANEL

Container Label